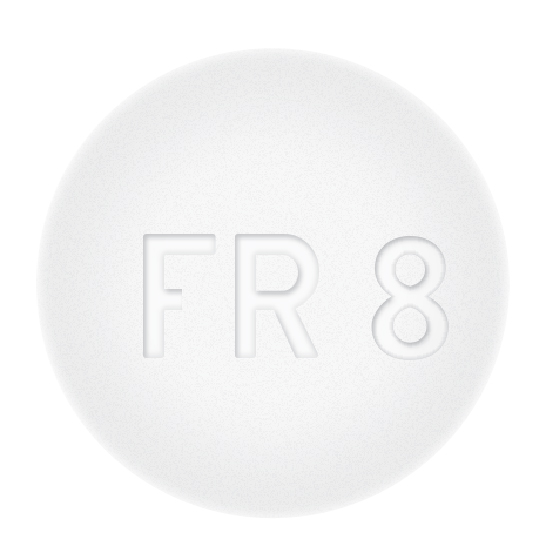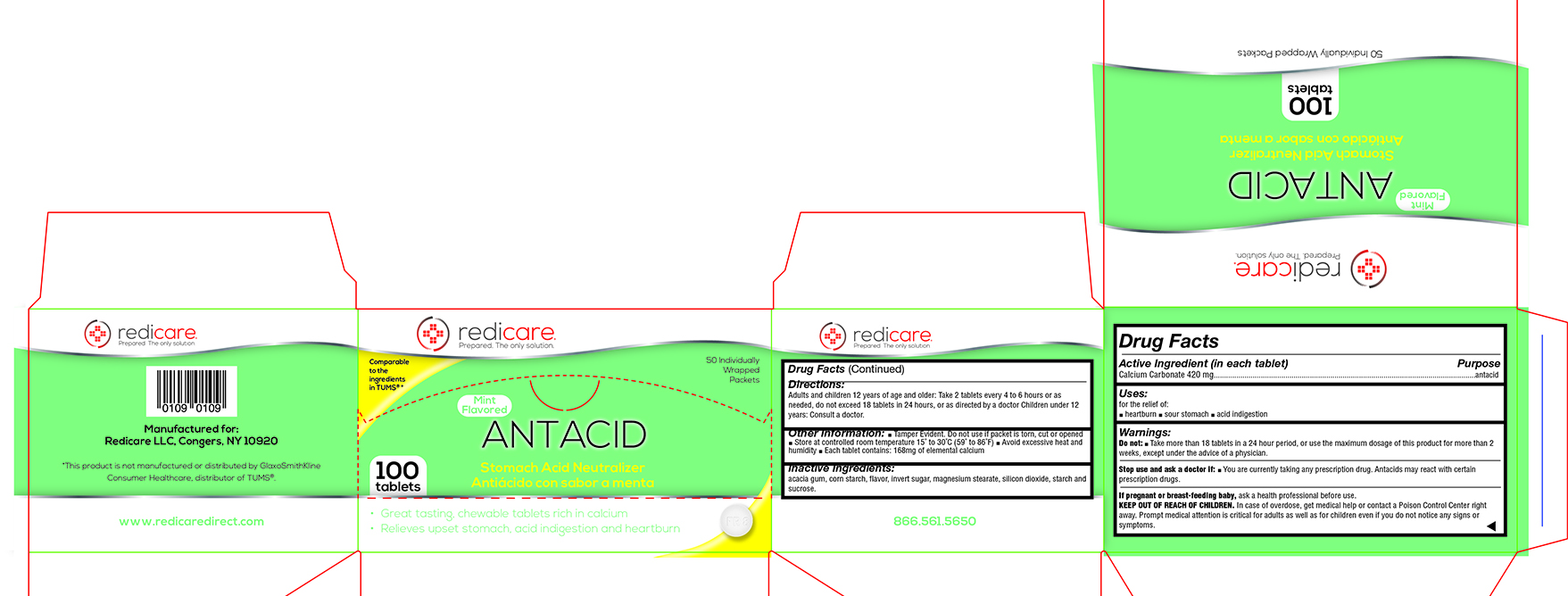 DRUG LABEL: Mint Flavored Antacid
NDC: 71105-303 | Form: TABLET, CHEWABLE
Manufacturer: Redicare LLC
Category: otc | Type: HUMAN OTC DRUG LABEL
Date: 20210702

ACTIVE INGREDIENTS: CALCIUM CARBONATE 420 mg/1 1
INACTIVE INGREDIENTS: STARCH, CORN; MAGNESIUM STEARATE; SUCROSE; SILICON DIOXIDE; MINT

Mint Antacid

Active Ingredient (in each tablet) Purpose

Calcium Carbonate 420 mg................................................................................................................................antacid

Uses:

for the relief of: ■ heartburn ■ sour stomach ■ acid indigestion

Warnings:

Do not: ■ Take more than 18 tablets in a 24 hour period, or use the maximum dosage of this product for more than 2 weeks, except under the advice of a physician

Stop use and ask a doctor if:

■ You are currently taking any prescription drug. Antacids may react with certain prescription drugs.

If pregnant or breast-feeding baby

ask a health professional before use.

KEEP OUT OF REACH OF CHILDREN.

In case of overdose, get medical help or contact a Poison Control Center right away. Prompt medical attention is critical for adults as well as for children even if you do not notice any signs or symptoms.

Directions:

Adults and children 12 years of age and older: Take 2 tablets every 4 to 6 hours or as needed, do not exceed 18 tablets in 24 hours, or as directed by a doctor Children under 12 years: Consult a doctor.

Other Information:

■ Tamper Evident. Do not use if packet is torn, cut or opened ■ Store at controlled room temperature 15˚ to 30˚C (59˚ to 86˚F) ■ Avoid excessive heat and humidity ■ Each tablet contains: 168mg of elemental calcium

Inactive Ingredients:

acacia gum, corn starch, flavor, invert sugar, magnesium stearate, silicon dioxide, starch and sucrose.